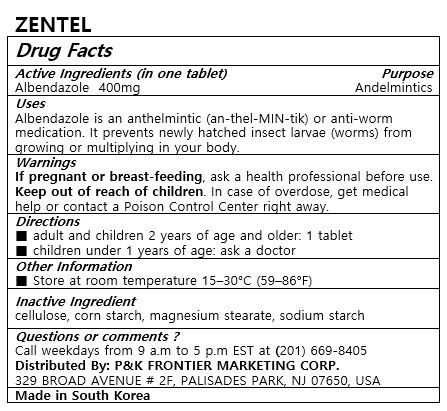 DRUG LABEL: ZENTEL
NDC: 72689-0036 | Form: TABLET
Manufacturer: OASIS TRADING
Category: otc | Type: HUMAN OTC DRUG LABEL
Date: 20190318

ACTIVE INGREDIENTS: ALBENDAZOLE 400 mg/1 1
INACTIVE INGREDIENTS: MAGNESIUM STEARATE

ACTIVE INGREDIENT

Albendazole

PURPOSE

Albendazole is an anthelmintic (an-thel-MIN-tik) or anti-worm medication. It prevents newly hatched insect larvae (worms) from growing or multiplying in your body.

Keep out of reach of children

INDICATIONS AND USAGE

■ adult and children 2 years of age and older: 1 tablet
■ children under 1 years of age: ask a doctor

WARNINGS

If pregnant or breast-feeding, ask a health professional before use.
Keep out of reach of children. In case of overdose, get medical help or contact a Poison Control Center right away.

INACTIVE INGREDIENT

cellulose, corn starch, magnesium stearate, sodium starch

DOSAGE AND ADMINISTRATION

For oral use only